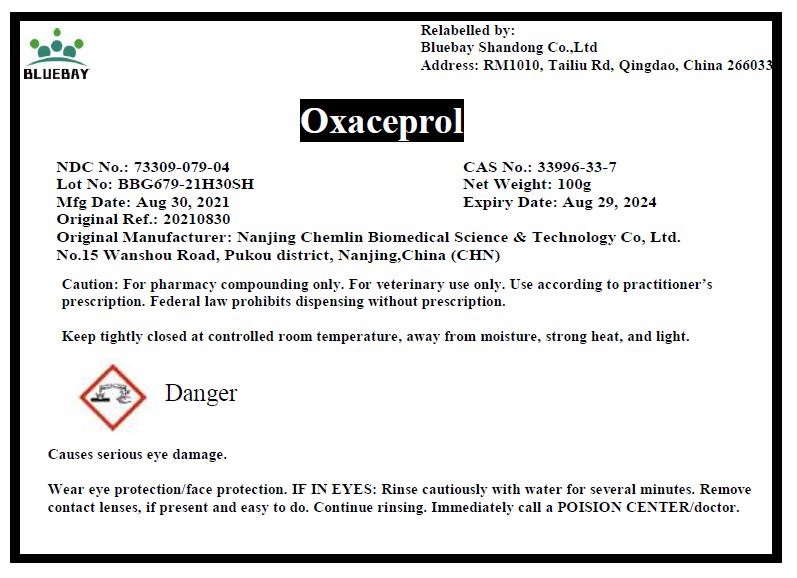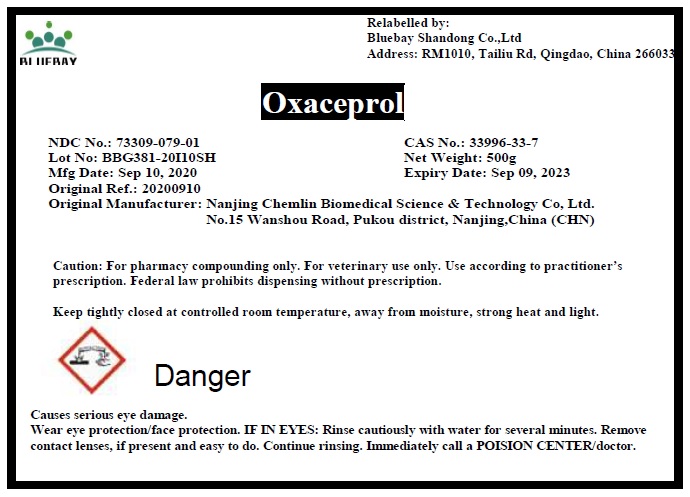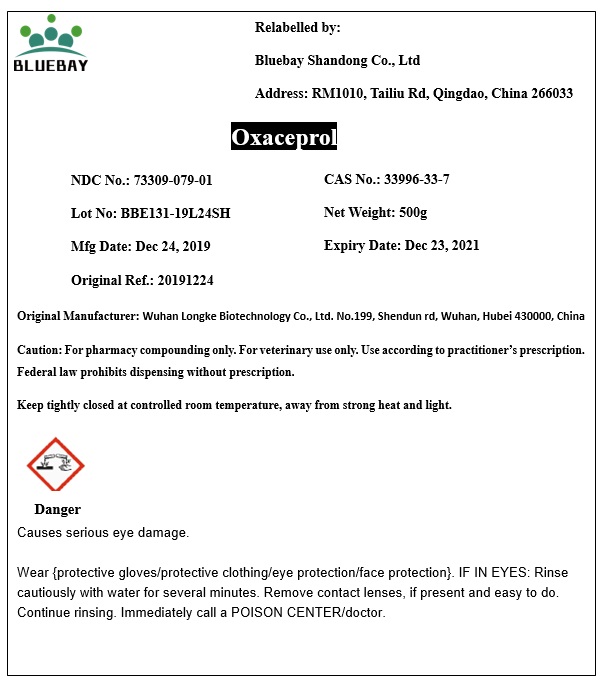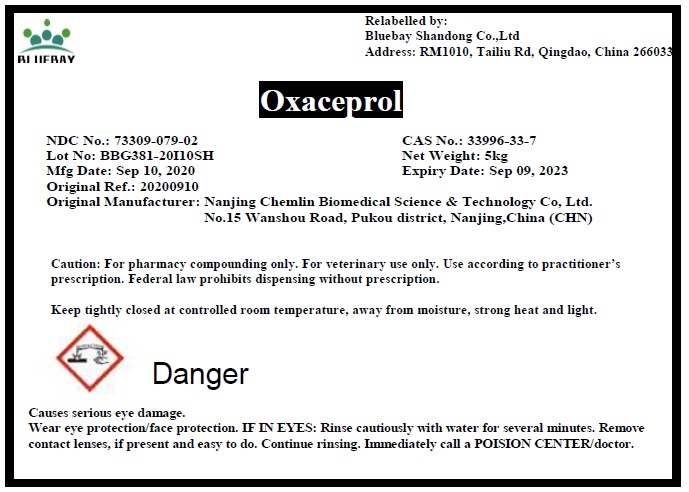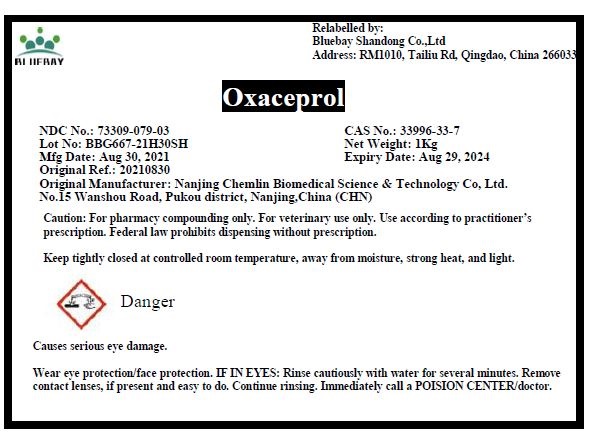 DRUG LABEL: Oxaceprol
NDC: 73309-079 | Form: POWDER
Manufacturer: BLUEBAY SHANDONG CO.,LTD
Category: other | Type: BULK INGREDIENT
Date: 20211231

ACTIVE INGREDIENTS: Oxaceprol 1 g/1 g

Oxaceprol